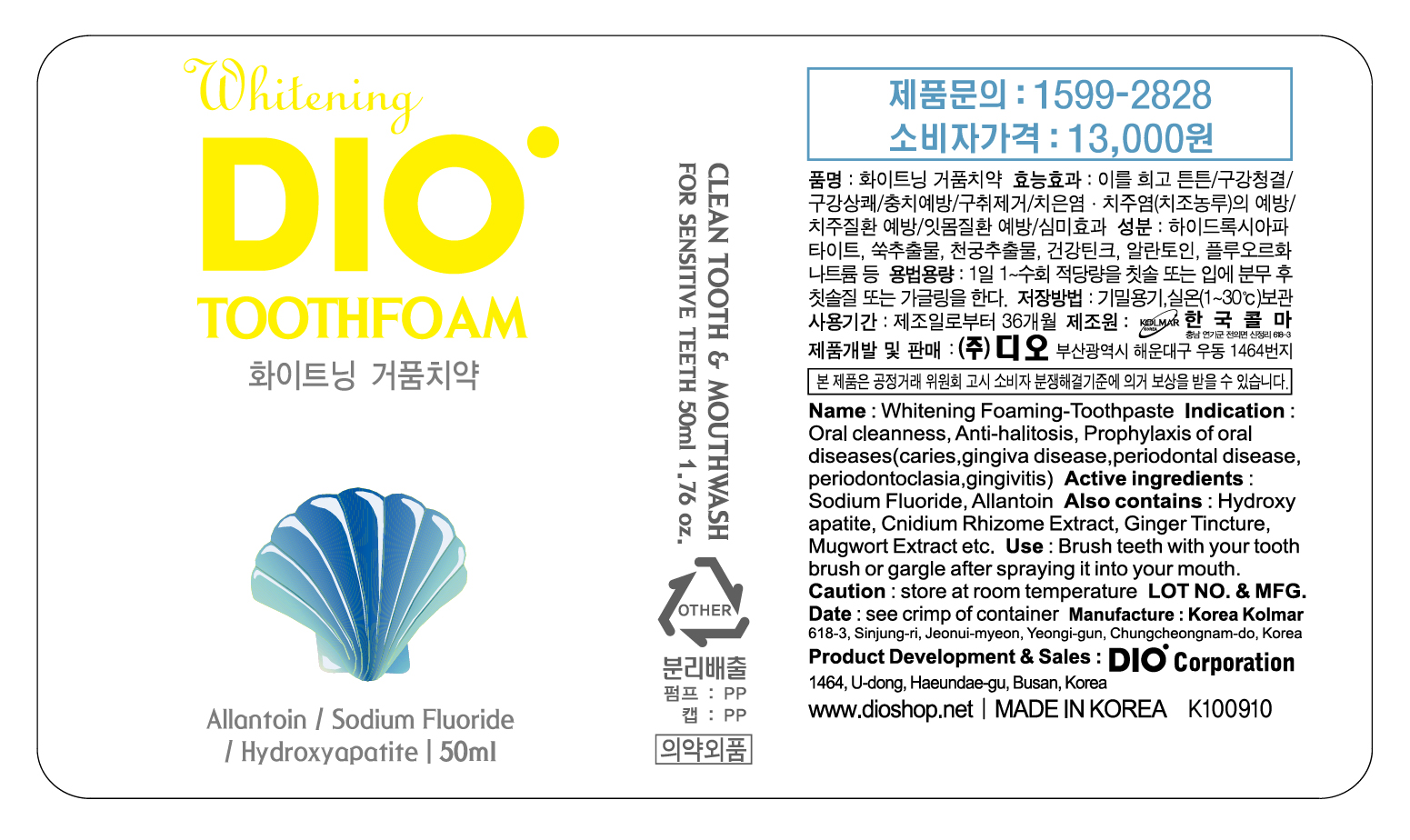 DRUG LABEL: Whitening Foaming-Toothpaste
NDC: 75902-2001 | Form: GEL, DENTIFRICE
Manufacturer: Dio Corporation
Category: otc | Type: HUMAN OTC DRUG LABEL
Date: 20111004

ACTIVE INGREDIENTS: SODIUM FLUORIDE 0.001 mL/1 mL; ALLANTOIN 0.0005 mL/1 mL
INACTIVE INGREDIENTS: ALCOHOL; SODIUM LAURYL SULFATE; XYLITOL; SACCHARIN SODIUM; GINGER; ARTEMISIA PRINCEPS LEAF; CNIDIUM OFFICINALE ROOT; MINT; METHYLPARABEN; WATER

Drug Facts

active ingredients: sodium fluoride, allantoin

INACTIVE INGREDIENT

inactive ingredients: ethanol sodium lauryl sulfact, xylitol, sodium saccharin, ginger, mugwort extract, cnidium extract, mint, methylparaben, water

PURPOSE

for dental care

keep out of reach of the children

INDICATIONS AND USAGE

brush teeth with your tooth brush or gargle after spraying it into your mouth

WARNINGS

store at room temperature

DOSAGE AND ADMINISTRATION

use when needed
dental use only